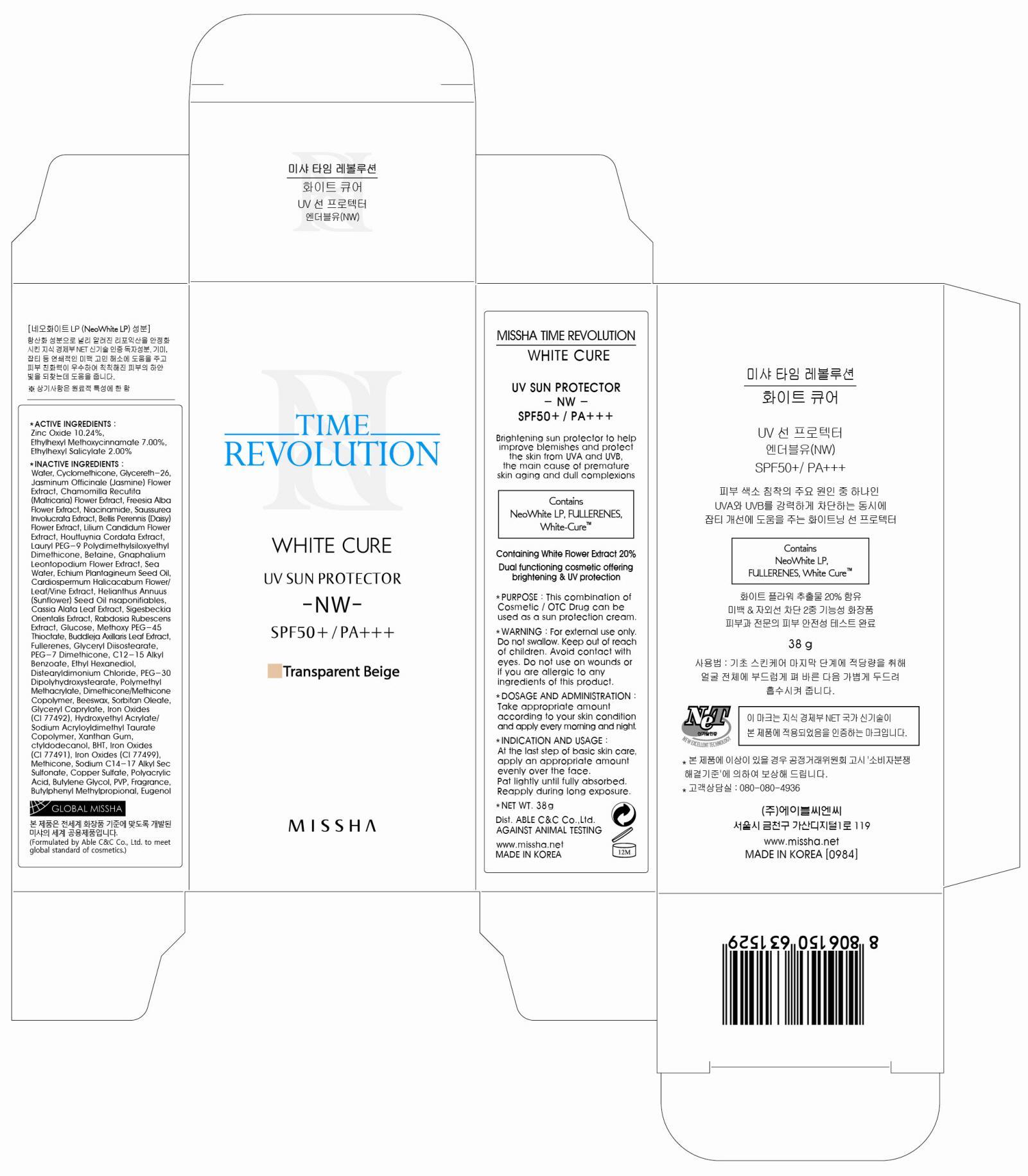 DRUG LABEL: MISSHA TIME REVOLUTION WHITE CURE UV SUN PROTECTOR
NDC: 13733-019 | Form: CREAM
Manufacturer: ABLE C&C CO., LTD.
Category: otc | Type: HUMAN OTC DRUG LABEL
Date: 20121030

ACTIVE INGREDIENTS: ZINC OXIDE 3.89 g/38 g; OCTINOXATE 2.66 g/38 g; OCTISALATE 0.76 g/38 g
INACTIVE INGREDIENTS: Water; Cyclomethicone; Glycereth-26; Niacinamide

ACTIVE INGREDIENT

ACTIVE INGREDIENTS: Zinc Oxide 10.24%, Ethylhexyl Methoxycinnamate 7.00%, Ethylhexyl Salicylate 2.00%

INACTIVE INGREDIENT

INACTIVE INGREDIENTS : Water, Cyclomethicone, Glycereth-26, Jasminum Officinale (Jasmine) Flower Extract, Chamomilla Recutita (Matricaria) Flower Extract, Freesia Alba Flower Extract, Niacinamide, Saussurea Involucrata Extract, Bellis Perennis (Daisy) Flower Extract, Lilium Candidum Flower Extract, Houttuynia Cordata Extract, Lauryl PEG-9 Polydimethylsiloxyethyl Dimethicone, Betaine, Gnaphalium Leontopodium Flower Extract, Sea Water, Echium Plantagineum Seed Oil, Cardiospermum Halicacabum Flower/Leaf/Vine Extract, Helianthus Annuus (Sunflower) Seed Oil Unsaponifiables, Cassia Alata Leaf Extract, Sigesbeckia Orientalis Extract, Rabdosia Rubescens Extract, Glucose, Methoxy PEG-45 Thioctate, Buddleja Axillaris Leaf Extract, Fullerenes, Glyceryl Diisostearate, PEG-7 Dimethicone, C12-15 Alkyl Benzoate, Ethyl Hexanediol, Distearyldimonium Chloride, PEG-30 Dipolyhydroxystearate, Polymethyl Methacrylate, Dimethicone/Methicone Copolymer, Beeswax, Sorbitan Oleate, Glyceryl Caprylate, Iron Oxides, Hydroxyethyl Acrylate/Sodium Acryloyldimethyl Taurate Copolymer, Xanthan Gum, Octyldodecanol, BHT, Methicone, Sodium C14-17 Alkyl Sec Sulfonate, Copper Sulfate, Polyacrylic Acid, Butylene Glycol, PVP, Fragrance, Butylphenyl Methylpropional, Eugenol

PURPOSE

PURPOSE: This combination of Cosmetic / OTC Drug can be used as a sun protection cream

WARNINGS

WARNING:
For external use only.
Do not swallow.
Keep out of reach of children.
Avoid contact with eyes.
Do not use on wounds or if you are allergic to any ingredients of this product.

KEEP OUT OF REACH OF CHILDREN

INDICATIONS AND USAGE

INDICATION AND USAGE:
At the last step of basic skin care, apply an appropriate amount evenly over the face.
Pat lightly until fully absorbed.
Reapply during long exposure.

DOSAGE AND ADMINISTRATION: Take appropriate amount according to your skin condition and apply every morning and night.